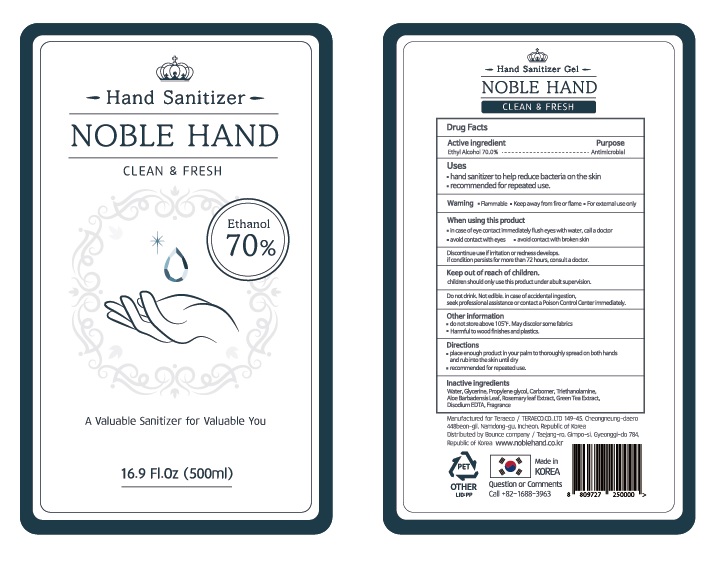 DRUG LABEL: Noble Hand
NDC: 77866-001 | Form: GEL
Manufacturer: BOUNCE COMPANY CO., LTD
Category: otc | Type: HUMAN OTC DRUG LABEL
Date: 20200515

ACTIVE INGREDIENTS: ALCOHOL 70 mL/100 mL
INACTIVE INGREDIENTS: PROPYLENE GLYCOL 1 mL/100 mL; ALOE VERA LEAF 0.01 mL/100 mL; ROSEMARY 0.01 mL/100 mL; EDETATE DISODIUM ANHYDROUS 0.015 mL/100 mL; GLYCERIN 1 mL/100 mL; WATER 27.245 mL/100 mL; CARBOMER 940 0.33 mL/100 mL; GREEN TEA LEAF 0.01 mL/100 mL; TROLAMINE 0.33 mL/100 mL

PACKAGE LABEL

Hand Clean Gel

Noble Hand

Ehtanol 70%

Cleaning with secondary water after first cleaning is better for cleaning